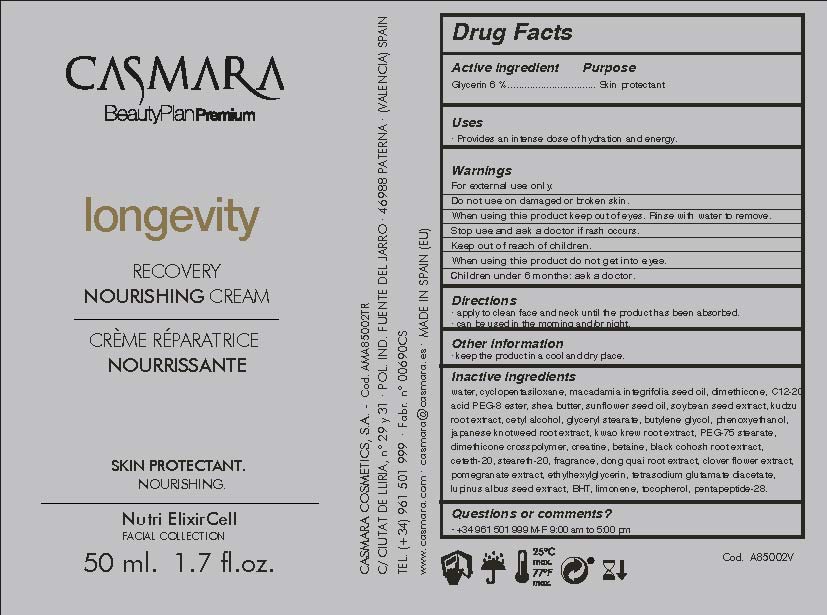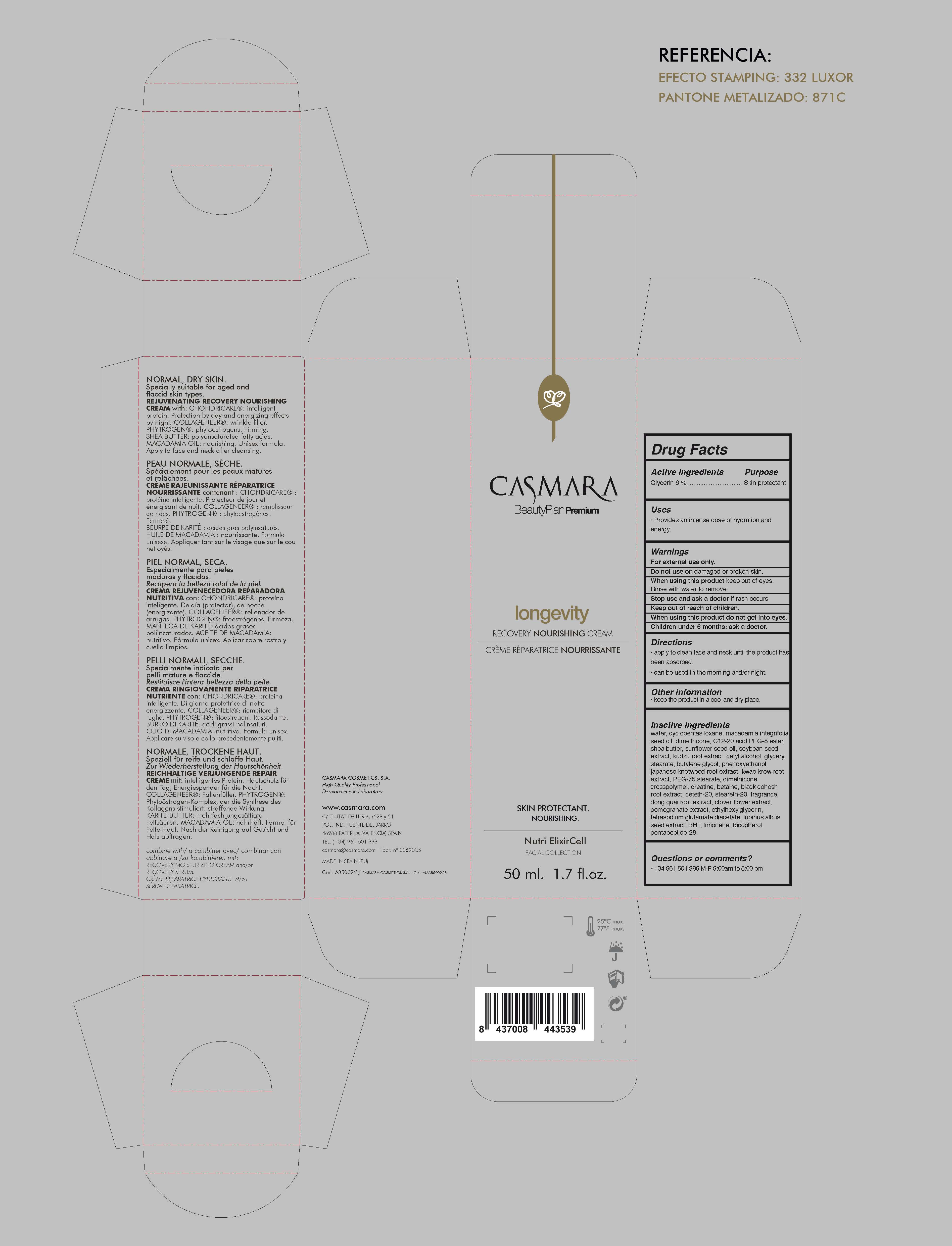 DRUG LABEL: Longevity Recovery Nourishing
NDC: 20151-099 | Form: CREAM
Manufacturer: Casmara Cosmetics, SA
Category: otc | Type: HUMAN OTC DRUG LABEL
Date: 20170330

ACTIVE INGREDIENTS: GLYCERIN 6 mg/1 mL; DIMETHICONE 3.36 mg/1 mL
INACTIVE INGREDIENTS: CETYL ALCOHOL 1.5 mg/1 mL; ETHYLHEXYLGLYCERIN 0.1 mg/1 mL; WATER 61.0949 mg/1 mL; CYCLOMETHICONE 5 4 mg/1 mL; PHENOXYETHANOL 0.9 mg/1 mL; MACADAMIA OIL 4 mg/1 mL; TETRASODIUM GLUTAMATE DIACETATE 0.094 mg/1 mL; SHEA BUTTER 2 mg/1 mL; TOCOPHEROL 0.004 mg/1 mL; SUNFLOWER OIL 1.918 mg/1 mL; LIMONENE, (+)- 0.014 mg/1 mL; SOYBEAN OIL 1.875 mg/1 mL; PUERARIA MONTANA VAR. LOBATA ROOT 0.875 mg/1 mL; GLYCERYL STEARATE SE 1.5 mg/1 mL; C12-20 ACID PEG-8 ESTER 3 mg/1 mL; BUTYLATED HYDROXYTOLUENE 0.02 mg/1 mL; PERSICARIA TINCTORIA LEAF 0.875 mg/1 mL; PEG-75 STEARATE 0.7 mg/1 mL; BETAINE 0.5 mg/1 mL; CREATINE 0.5 mg/1 mL; CETETH-20 0.3 mg/1 mL; STEARETH-20 0.3 mg/1 mL; PUERARIA CANDOLLEI VAR. MIRIFICA ROOT 0.875 mg/1 mL; BUTYLENE GLYCOL 1.025 mg/1 mL; PENTAPEPTIDE-31 0.000025 mg/1 mL; LUPINUS ALBUS SEED 0.08 mg/1 mL; CAULOPHYLLUM ROBUSTUM ROOT 0.375 mg/1 mL; DIMETHICONE CROSSPOLYMER (450000 MPA.S AT 12% IN CYCLOPENTASILOXANE) 0.64 mg/1 mL; RED CLOVER 0.125 mg/1 mL; ANGELICA SINENSIS ROOT 0.125 mg/1 mL; POMEGRANATE 0.125 mg/1 mL

Longevity Recovery Nourishing Cream

ACTIVE INGREDIENTS PURPOSE

Glycerin 6%.................... Skin Protectant

Warnings

For external use only.

Do not use on damaged or broken skin.

When using this product keep our of the eyes. Rinse with water to remove.

Stop use and ask a doctor if rash occurs.

Keep out of reach of children.

Whhen using this product do not get into eyes.

Children under 6 months: as a doctor.

WARNINGS

Stop use and ask a doctor if rash occurs

Children under 6 months: ask a doctor

Warnings

Keep out of reach of children

Questions or comments?

+ 34 961 501 999 M-F 9:00 am to 5:00 pm

Other Information

. keep the product in a cool and dry place

Directions

. apply to clean face and neck until the product has been absorbed

. can be used in the morning and/or night

DOSAGE AND ADMINISTRATION

. apply to clean face and neck until the product has been absorbed

. can be used in the morning and/or night

Uses

. provides an intense dose of hydration and energy

Inactive Ingredients

Water, Cyclopentasiloxane, Macadamia integrifolia seed oil, Dimethicone, C12-20 acid PEG-8 ester, Shea butter, Sunflower seed oi, Soybean seed extract, Kudzu root extract, Cetyl alcohol, Glyceryl stearate, Butylene glycol, Phenoxyethanol, Japanese knotweed root extract, Kwao krew root extract, PEG-75 stearate, Dimethicone crosspolymer, Creatine, Betaine, Black cohosh root extract Ceteth-20, Steareth-20, Fragrance, Dong quai root extract, Clover flower extract, Pomegranate extract, Ethylhexylglycerin, Tetrasodium glutamate diacetate, Lupinus albus seed extract, BHT, Limonene, Tocopherol, Pentapeptide-28

Uses

. provides an intense dose of hydration and energy